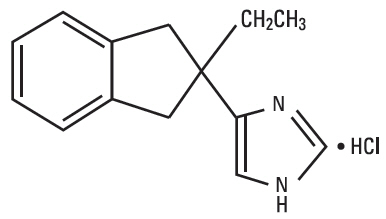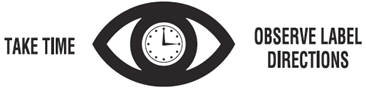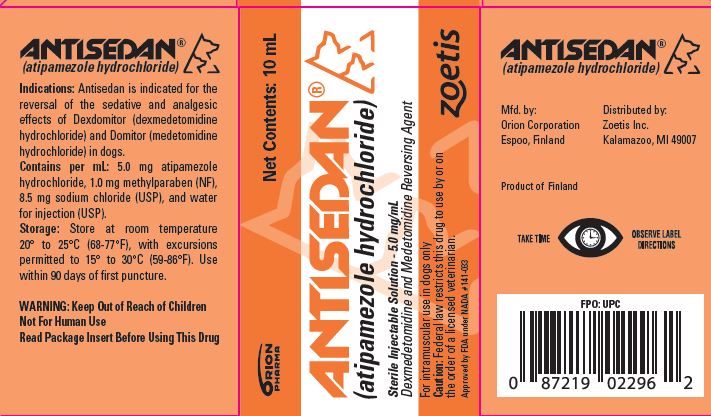 DRUG LABEL: Antisedan
NDC: 54771-6293 | Form: INJECTION, SOLUTION
Manufacturer: Zoetis Inc.
Category: animal | Type: PRESCRIPTION ANIMAL DRUG LABEL
Date: 20200618

ACTIVE INGREDIENTS: atipamezole hydrochloride 5 mg/1 mL
INACTIVE INGREDIENTS: methylparaben 1 mg/1 mL; sodium chloride 8.5 mg/1 mL

ANTISEDAN®
(atipamezole hydrochloride)

Sterile Injectable Solution - 5.0 mg/mL

Dexmedetomidine and Medetomidine Reversing Agent

For intramuscular use in dogs only

CAUTION

Federal law restricts this drug to use by or on the order of a licensed veterinarian.

DESCRIPTION

ANTISEDAN (atipamezole hydrochloride) is a synthetic α2-adrenergic antagonist.

The chemical name is 4-(2-ethyl-2,3-dihydro-1H-inden-2-yl)-1H-imidazole hydrochloride.

The molecular formula is C14H16N2 • HCl and structural formula is:

Each mL of ANTISEDAN contains 5.0 mg atipamezole hydrochloride, 1.0 mg methylparaben (NF), 8.5 mg sodium chloride (USP), and water for injection (USP).

INDICATIONS

ANTISEDAN is indicated for the reversal of the sedative and analgesic effects of DEXDOMITOR (dexmedetomidine hydrochloride), and DOMITOR (medetomidine hydrochloride) in dogs.

DOSAGE AND ADMINISTRATION

ANTISEDAN is administered intramuscularly (IM) for reversal of sedation and analgesia regardless of the route used for DEXDOMITOR or DOMITOR. The atipamezole dose for the reversal of IV DEXDOMITOR or DOMITOR is 3750 mcg/m^2. The atipamezole dose for the reversal of IM DEXDOMITOR or DOMITOR is 5000 mcg/m^2.

The dosage of ANTISEDAN is calculated based on body surface area. Use the following tables to determine the correct injection volume or the correct ANTISEDAN dosage on the basis of kilograms of body weight.

Note that the mcg/kg dosage decreases as body weight increases.

Table 1: Atipamezole dosing for reversal of IV dexmedetomidine- or medetomidine-induced sedation/analgesia:
Dose table for ANTISEDAN (3750 mcg/m^2) when dexmedetomidine or medetomidine is given IV
For # lbs | For # kg | dose = mcg/kg | volume = mL ANTISEDAN
4-7 | 2-3 | 300 | 0.1
7-9 | 3-4 | 250 | 0.15
9-11 | 4-5 | 230 | 0.2
11-22 | 5-10 | 200 | 0.3
22-33 | 10-15 | 170 | 0.4
33-44 | 15-20 | 150 | 0.5
44-55 | 20-25 | 140 | 0.6
55-66 | 25-30 | 130 | 0.7
66-81 | 30-37 | 120 | 0.8
81-99 | 37-45 | 110 | 0.9
99-110 | 45-50 | 105 | 1.0
110-132 | 50-60 | 100 | 1.1
132-143 | 60-65 | 95 | 1.2
143-165 | 65-75 | 93 | 1.3
165-176 | 75-80 | 91 | 1.4
>176 | >80 | 90 | 1.5

Table 2: Atipamezole dosing for reversal of IM dexmedetomidine- or medetomidine-induced sedation/analgesia:
Dose table for ANTISEDAN (5000 mcg/m^2) when dexmedetomidine or medetomidine is given IM
For # lbs | For # kg | dose = mcg/kg | volume = mL ANTISEDAN
4-7 | 2-3 | 400 | 0.15
7-9 | 3-4 | 350 | 0.2
9-11 | 4-5 | 300 | 0.3
11-22 | 5-10 | 250 | 0.4
22-29 | 10-13 | 230 | 0.5
29-33 | 13-15 | 210 | 0.6
33-44 | 15-20 | 200 | 0.7
44-55 | 20-25 | 180 | 0.8
55-66 | 25-30 | 170 | 0.9
66-73 | 30-33 | 160 | 1.0
73-81 | 33-37 | 150 | 1.1
81-99 | 37-45 | 145 | 1.2
99-110 | 45-50 | 140 | 1.3
110-121 | 50-55 | 135 | 1.4
121-132 | 55-60 | 130 | 1.5
132-143 | 60-65 | 128 | 1.6
143-154 | 65-70 | 125 | 1.7
154-176 | 70-80 | 123 | 1.8
>176 | >80 | 120 | 1.9

CONTRAINDICATIONS

Since atipamezole is always used concomitantly with dexmedetomidine or medetomidine, it should not be used in dogs with the following conditions: cardiac disease, respiratory disorders, liver or kidney diseases, dogs in shock, severely debilitated dogs, or dogs stressed due to extreme heat, cold or fatigue.

Administration of atipamezole is contraindicated in dogs with a known hypersensitivity to the drug.

HUMAN WARNINGS

Not for human use. Keep out of reach of children.

Atipamezole hydrochloride can be absorbed and may cause irritation following direct exposure to skin, eyes, or mouth. In case of accidental eye exposure, flush with water for 15 minutes. In case of accidental skin exposure, wash with soap and water. Remove contaminated clothing.

If irritation or other adverse reaction occurs (for example, increased heart rate, tremor, muscle cramps), seek medical attention.

In case of accidental oral exposure or injection, seek medical attention. Caution should be used while handling and using filled syringes.

Users with cardiovascular disease (for example, hypertension or ischemic heart disease) should take special precautions to avoid any exposure to this product.

The safety data sheet (SDS) contains more detailed occupational safety information.
To report adverse reactions in users or to obtain a copy of the SDS for this product call 1-888-963-8471.

Note to Physician: This product contains an alpha2-adrenergic antagonist.

PRECAUTIONS

1. Handling:

ANTISEDAN can produce an abrupt reversal of sedation; therefore, dogs that have recently received ANTISEDAN should be handled with caution. The potential for apprehensive or aggressive behavior should be considered in the handling of dogs emerging from sedation, especially in dogs predisposed to nervousness or fright. Also, avoid situations where a dog might fall.

2. Sedation relapse:

While atipamezole does reverse the clinical signs associated with medetomidine or dexmedetomidine sedation, complete physiologic return to pretreatment status may not be immediate or may be temporary, and dogs should be monitored for sedation relapse. Sedation relapse is more likely to occur in dogs that receive an alpha2-agonist by the IV route, compared to dogs that are sedated using the IM route. Animals should be monitored closely for persistent hypothermia, bradycardia, and depressed respiration, until signs of recovery persist.

3. Analgesia reversal:

Atipamezole reverses analgesic effects as well as sedative effects. Additional procedures for the control of pain may be required.

4. Debilitated dogs:

The safety of atipamezole has not been evaluated in dogs with compromised health. Geriatric, debilitated, and ill dogs are more likely to experience adverse reactions associated with the administration of alpha2-antagonists (as well as alpha2-agonists). Dogs with abnormalities associated with the cardiovascular system are especially at risk.

5. Breeding dogs:

ANTISEDAN has not been evaluated in breeding dogs; therefore, the drug is not recommended for use in pregnant or lactating dogs, or in dogs intended for breeding.

6. Minimum age and weight:

ANTISEDAN has not been evaluated in dogs less than four months of age or in dogs weighing less than 4.4 lbs (2 kg).

ADVERSE REACTIONS

Occasional vomiting may occur. At times, a period of excitement or apprehensiveness may be seen in dogs treated with atipamezole. Other effects of atipamezole include hypersalivation, diarrhea, and tremors.

CLINICAL PHARMACOLOGY

Atipamezole is a potent alpha2-antagonist which selectively and competitively inhibits alpha2-adrenergic receptors. The result of atipamezole administration in the dog is the rapid recovery from the sedative and analgesic effects produced by the alpha2-adrenergic agonists dexmedetomidine or medetomidine. Atipamezole does not reverse the effects of other classes of sedatives, anesthetics, or analgesics.

Atipamezole is rapidly absorbed following intramuscular injection; maximum serum concentration is reached in approximately 10 minutes. Onset of arousal is usually apparent within 5 to 10 minutes of injection, depending on the depth and duration of dexmedetomidine- or medetomidine-induced sedation. Elimination half-life from serum is less than 3 hours. Atipamezole undergoes extensive hepatic biotransformation, with excretion of metabolites primarily in urine.

Dexmedetomidine or medetomidine activation of peripheral and central alpha2-adrenergic receptors induces a pattern of pharmacological responses that include sedation, reduction of anxiety, analgesia, and bradycardia.

Blood pressure is initially increased due to peripheral vasoconstriction and thereafter drops to normal or slightly below normal levels. A transient, decrease in systolic blood pressure occurs immediately after administration of atipamezole to dexmedetomidine- or medetomidine-sedated dogs, followed by a transient increase in arterial pressure within 10 minutes compared to pre-atipamezole levels. This is the opposite of the response to alpha2-agonist treatment, and is probably due to atipamezole-induced peripheral vasodilation.

Atipamezole administration rapidly abolishes dexmedetomidine- or medetomidine-induced bradycardia, usually within 3 minutes. The magnitude of the effect of atipamezole on heart rate is greater when dexmedetomidine is administered intravenously compared to intramuscularly. Dogs receiving medetomidine or IM dexmedetomidine may not return to pre-sedative heart rates after atipamezole administration and some dogs briefly show heart rate elevations above baseline. Respiratory rate increases following atipamezole injection.

EFFECTIVENESS

One hundred and nine dogs received atipamezole in the field study (55 dogs received the reversal agent following dexmedetomidine; 54 following medetomidine). The mean age was 5.9 years and ranged between 17 weeks and 16 years. The mean weight was 45.5 lbs (20.7 kg), ranging from 4.8 lbs to 117 lbs (2.2 kg to 53.2 kg). Atipamezole was administered by the IM route of administration, within a range of 39-57 minutes after administration of either dexmedetomidine (IV and IM) or medetomidine (IV and IM).

Atipamezole reversed the effects of dexmedetomidine and medetomidine in all cases. In dexmedetomidine treated dogs, the onset of reversal was evident within 5 minutes after administration of atipamezole (57% could stand). Within 15 minutes, 96% of dexmedetomidine treated dogs were standing, 92% responded normally to sound, 86% had a normal muscle tone of jaw, and >90% had a normal pedal reflex response. Responses in dogs treated with medetomidine were similar or slightly later.

Following atipamezole, heart rate increased between 0 and 5 minutes following either alpha2-agonist (IV dexmedetomidine dogs had heart rates from 60 to 85 bpm, and IV medetomidine dogs from 51 to 67 bpm; IM dexmedetomidine dogs had heart rates from 45 to 73 bpm, and IM medetomidine dogs from 52 to 79 bpm). Bradycardia resolved more slowly in the IM treatment groups. The body temperature remained at the same level during the 120 minutes of follow-up after atipamezole administration. Respiratory rates increased toward normal between 0 and 5 minutes after the administration of atipamezole in all treatment groups. Mucous membranes were described as normal after 5 minutes in 91% of dexmedetomidine dogs (IV or IM). By 120 minutes, 96% were normal (after IV dexmedetomidine) or 100% were normal (after IM dexmedetomidine). Many physiological responses were slightly slower to return toward normal when dogs were treated with medetomidine IV or IM.

No adverse events were reported in the atipamezole treated dogs.

ANIMAL SAFETY

Atipamezole was tolerated in healthy dogs receiving 10X the recommended dose and in dogs receiving repeated doses at 1, 3, and 5X the recommended dose, in the absence of an alpha2-agonist. Signs were dose-related and included excitement, panting, trembling, vomiting, soft or liquid feces and scleral injection. At 10X the recommended dose, increases in creatine kinase, AST, and ALT were noted. Creatine kinase also increased in 3 (of 6) dogs in the 3X treatment group. Localized skeletal muscle injury was seen at the injection site but no associated clinical signs or complications were observed. Dogs receiving the recommended atipamezole dose in the absence of medetomidine or dexmedetomidine exhibited no adverse clinical signs. In additional safety studies, adverse events were absent up to the 3X dose of atipamezole when its administration followed medetomidine or dexmedetomidine sedation.

In a separate safety study using a crossover design, 5 dogs received atipamezole after dexmedetomidine (IV and IM). Dexmedetomidine's effects on blood pressure, heart rate, respiratory rate, and cardiac conduction times were reversed by atipamezole. However, heart rate and cardiac conduction times did not return to predexmedetomidine values. Heart rate increases after atipamezole were closer to baseline values in dogs treated with dexmedetomidine IV (compared to IM).

STORAGE INFORMATION

Store at room temperature 20° to 25°C (68-77°F), with excursions permitted to 15° to 30°C (59-86°F). Use within 90 days of first puncture.

HOW SUPPLIED

ANTISEDAN is supplied in 10-mL, multidose vials containing 5.0 mg of atipamezole hydrochloride per mL.

Approved by FDA under NADA # 141-033

Antisedan®, Dexdomitor®, and Domitor® are trademarks of Orion Corporation.

Revised: April 2019

Developed and manufactured by:
ORION
PHARMA
Orion Corporation
Espoo, Finland

Distributed by:
Zoetis Inc.
Kalamazoo, MI 49007

Product of Finland

107237-8